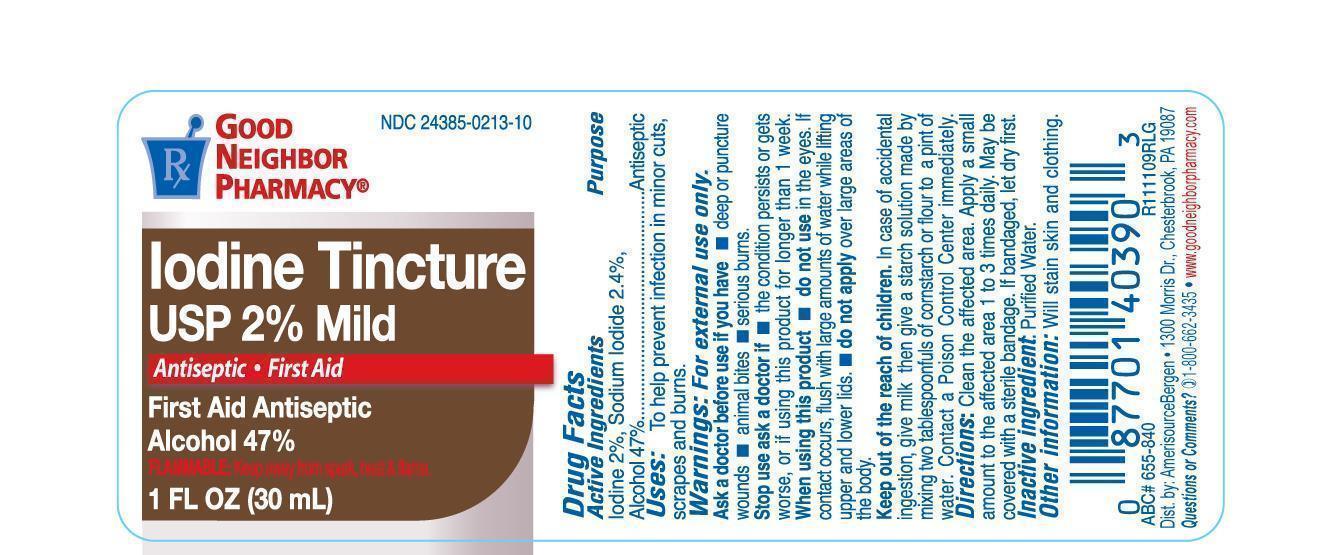 DRUG LABEL: GNP Idoinde Tincture 2% Mild
NDC: 24385-213 | Form: LIQUID
Manufacturer: Amerisource Bergen
Category: otc | Type: HUMAN OTC DRUG LABEL
Date: 20231214

ACTIVE INGREDIENTS: IODINE 20 mg/1 mL; SODIUM IODIDE 20.4 mg/1 mL; ALCOHOL 470 mg/1 mL
INACTIVE INGREDIENTS: WATER

GNP Iodine Tincture USP 2% Mild

Drug facts

Active Ingredients

Iodine 2%

Sodium iodide 2.4%

Alcohol 47%

Purpose

Antiseptic

Uses:

To help prevent infection in minor cuts, scrapes and burns.

Warnings:

For external use only

Ask a doctor before use if you have

- deep or puncture wounds.
- animal bites.
- serious burns.

Stop use and ask a doctor if

condition persists or gets worse, or if using this product for longer than 1 week.

When using this product.

Do not use in eyes. If contact occurs, flush with large amounts of water while lifting upper and lower eyelids.

Do not apply over large areas of the body.

Keep out of reach ofchildren

In case of accidental ingestion, give milk then give a starch solution made by mixing two tablespoonfuls of cornstarch or flour to a pint of water. Contact a Poison Control Center immediately.

Directions:

Clean the affected area. Apply a small amount to the affeted area 1 to 3 times daily. May be covered with sterile bandage. If bandaged, let dry first.

Inactive ingredient:

Purified Water.

Other information:

Will stain skin and clothing

Dist. by: AmerisourceBergen

1300 Morris Dr., Chesterbrook, PA 19087

Questions or Comments?

1-800-662-3435 www.goodneighborpharmacy.com

Principal Display Panel

Good Neighbor Pharmacy NDC 24385-0213-10

Iodine Tincture USP 2% Mild

Antiseptic First Aid

First Aid Antiseptic

Alcohol 47%

FLAMMABLE: Keep away from sparks, heal & flame.

1 FL OZ (30 mL)